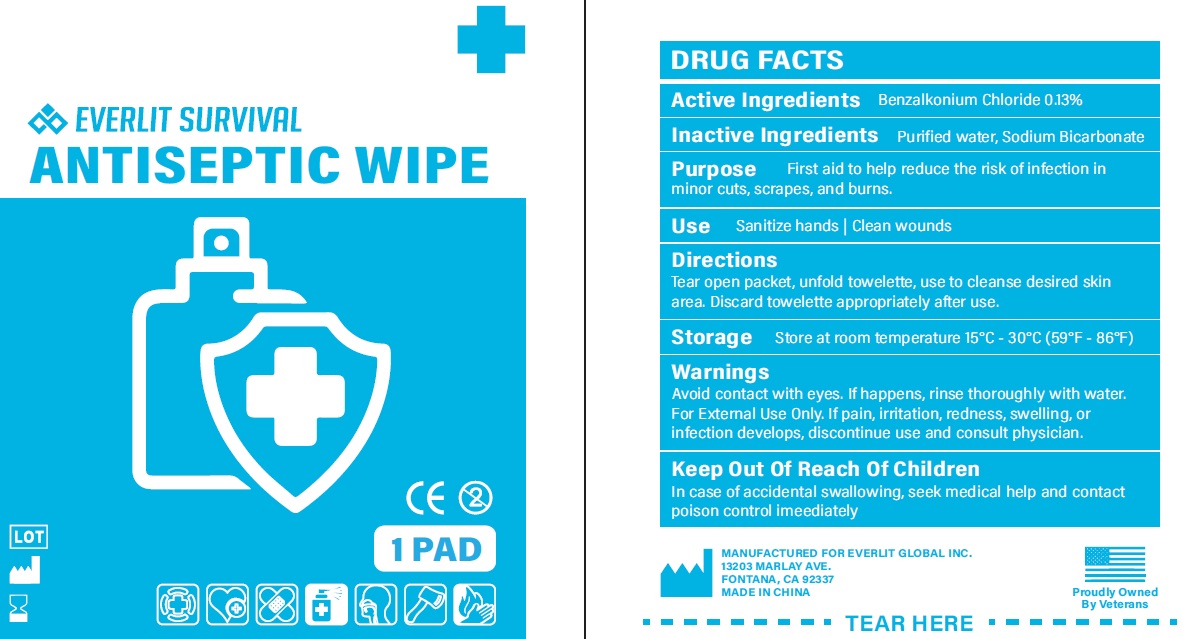 DRUG LABEL: Antiseptic wipe
NDC: 72459-015 | Form: SOLUTION
Manufacturer: Yiwu Ori-Power Medtech Co.,Ltd.
Category: otc | Type: HUMAN OTC DRUG LABEL
Date: 20260101

ACTIVE INGREDIENTS: BENZALKONIUM CHLORIDE 1.3 mg/1 g
INACTIVE INGREDIENTS: WATER; SODIUM BICARBONATE

EVERLIT SURVIVAL Antiseptic wipe

Active Ingredients

Benzalkonium Chloride 0.13%

Purpose

First aid to help reduce the risk of infection in minor cuts, scrapes, and burns.

Inactive Ingredients

Purfied water, Sodium Bicarbonate

Use

Sanitize hands Clean wounds

Directions

Tear open packet, unfold towelette, use to cleanse desired skin area. Discard towelette appropriately after use.

Storage

Store at room temperature 15°C - 30°C (59°F - 86°F).

Warnings

Avoid contact with eyes. If happens, rinse thoroughly with water. For External Use Only. If pain, irritation, redness, swelling, or infection develops, discontinue use and consult physician.

Keep Out Of Reach Of Children

In case of accidental swallowing, seek medical help and contact poison control imeediately